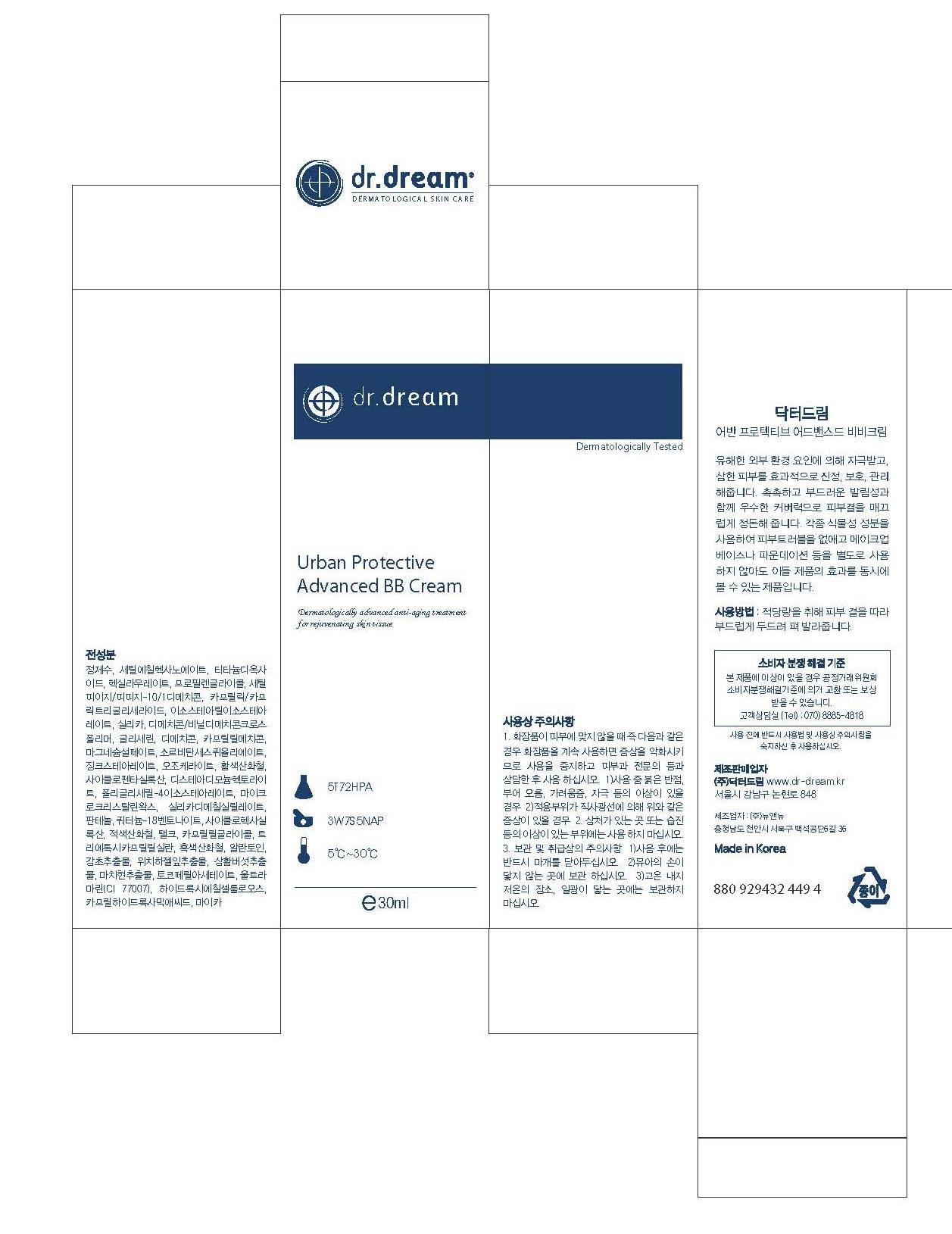 DRUG LABEL: Dr. Dream Urban Protective Advanced BB
NDC: 53077-8001 | Form: CREAM
Manufacturer: Dr. Dream Inc
Category: otc | Type: HUMAN OTC DRUG LABEL
Date: 20120925

ACTIVE INGREDIENTS: WITCH HAZEL 0.1 mg/100 mL
INACTIVE INGREDIENTS: MUSA BASJOO WHOLE; ACETYL HEXAPEPTIDE-8; PALMITOYL OLIGOPEPTIDE; PALMITOYL TETRAPEPTIDE-7; POLYSORBATE 60; GLYCERIN; CAPRYLHYDROXAMIC ACID; ADENOSINE; AMMONIUM ACRYLOYLDIMETHYLTAURATE/VP COPOLYMER; NEOPENTYL GLYCOL; BLACK OLIVE; SODIUM CHONDROITIN SULFATE (PORCINE; 5500 MW); LAVANDULA ANGUSTIFOLIA FLOWERING TOP; CYMBOPOGON SCHOENANTHUS OIL; ABIES SIBIRICA LEAF OIL; ORANGE; AMYRIS BALSAMIFERA OIL; CLARY SAGE OIL; LECITHIN, SOYBEAN; SODIUM PHOSPHATE; HYALURONATE SODIUM; THIOREDOXIN; PREZATIDE COPPER; PALMITOYL PENTAPEPTIDE-4; GLYCINE; GLUTAMINE; LYSINE; LEUCINE; METHIONINE; VALINE; SERINE; CYSTEINE; CYSTINE; ASPARAGINE; ALANINE; ARGININE; ORNITHINE; ISOLEUCINE; TYROSINE; THREONINE; TRYPTOPHAN; PHENYLALANINE; PROLINE; HISTIDINE

Drug Facts

ACTIVE INGREDIENT

witch hazel

INACTIVE INGREDIENT

water, butylene glycol, glycerin, cetyl ethylhexanoate, titanium dioxide, hexyl laurate, cetyl peg/ppg-10/1 dimethicone, caprylic/capric triglyceride, isostearyl isostearate, silica, dimethicone/'vinyl dimethicone crosspolymer, dimethicone, caprylyl methicone, magnesium sulfate, sorbitan sesquioleate, zinc stearate, ozokerite, iron oxides, cyclopentasiloxane, disteardimonium hectorite, polyglyceryl-4 isostearate, microcrystalline, wax, silica dimethyl silylate, panthenol, quaternium-18 bentinite, cyclohexasiloxane, CI 77491, talc, caprylyl glycol, triethoxycaprylylsilane, ci 77499, allantoin, licorice root extract, phellinus linteus extract, portulaca oleracea extract, tocopheryl acetate, ci 77003, hydroxyethylcellulose, caprylhydroxamic acid, mica

PURPOSE

general care

keep out of reach of the children

INDICATIONS AND USAGE

Take out the proper amount and spread it out over the face evenly after applying your basic makeup.

When using this product
- keep out of eyes, ears, and mouth. If contact occurs, rinse with plenty of cold water right away and contact a physician. If swallowing, drink plenty of water and contact a physician

DOSAGE AND ADMINISTRATION

for external use only